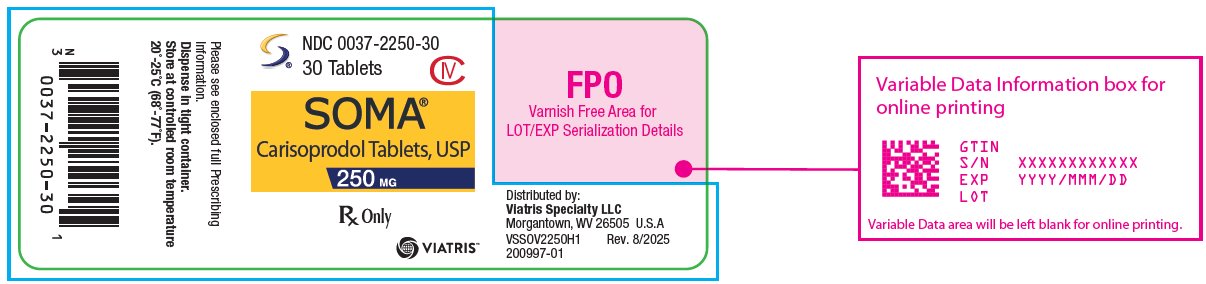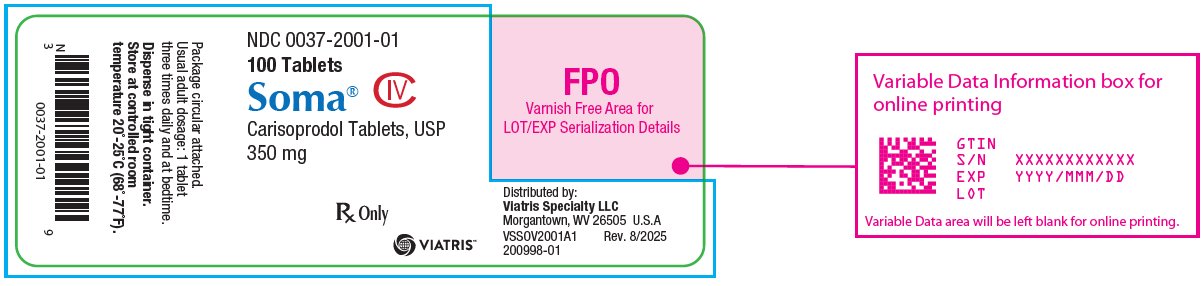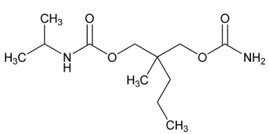 DRUG LABEL: Soma
NDC: 0037-2250 | Form: TABLET
Manufacturer: Viatris Specialty LLC
Category: prescription | Type: HUMAN PRESCRIPTION DRUG LABEL
Date: 20250829
DEA Schedule: CIV

ACTIVE INGREDIENTS: CARISOPRODOL 250 mg/1 1

HIGHLIGHTS OF PRESCRIBING INFORMATION

These highlights do not include all the information needed to use SOMA safely and effectively. See full prescribing information for SOMA.
SOMA (carisoprodol) tablets for oral use, CIV
Initial U.S. Approval: 1959

1 INDICATIONS AND USAGE

SOMA is a muscle relaxant indicated for the relief of discomfort associated with acute, painful musculoskeletal conditions in adults. (1)
Limitations of Use

- Should only be used for acute treatment periods up to two or three weeks (1)

2 DOSAGE AND ADMINISTRATION

- Recommended dose is 250 mg to 350 mg three times a day and at bedtime. (2)

3 DOSAGE FORMS AND STRENGTHS

Tablets: 250 mg, 350 mg (3)

4 CONTRAINDICATIONS

- Acute intermittent porphyria (4)
- Hypersensitivity reactions to a carbamate such as meprobamate (4)

5 WARNINGS AND PRECAUTIONS

- Due to sedative properties, may impair ability to perform hazardous tasks such as driving or operating machinery (5.1)
- Additive sedative effects when used with other CNS depressants including alcohol (5.1)
- Cases of abuse, dependence and withdrawal (5.2, 9.2, 9.3)
- Seizures (5.3)

6 ADVERSE REACTIONS

Most common adverse reactions (incidence > 2%) are drowsiness, dizziness, and headache (6.1)

To report SUSPECTED ADVERSE REACTIONS, contact Viatris at 1-877-446-3679 (1-877-4-INFO-RX) or FDA at 1-800-FDA-1088 or www.fda.gov/medwatch.

7 DRUG INTERACTIONS

CNS depressants (e.g., alcohol, benzodiazepines, opioids, tricyclic antidepressants) - additive sedative effects (5.1, 7.1)

FULL PRESCRIBING INFORMATION

1 INDICATIONS AND USAGE

SOMA is indicated for the relief of discomfort associated with acute, painful musculoskeletal conditions in adults.

Limitation of Use

SOMA should only be used for short periods (up to two or three weeks) because adequate evidence of effectiveness for more prolonged use has not been established and because acute, painful musculoskeletal conditions are generally of short duration [see Dosage and Administration (2)].

2 DOSAGE AND ADMINISTRATION

The recommended dose of SOMA is 250 mg to 350 mg three times a day and at bedtime. The recommended maximum duration of SOMA use is up to two or three weeks.

3 DOSAGE FORMS AND STRENGTHS

250 mg Tablets: round, convex, white tablets, inscribed with SOMA 250

350 mg Tablets: round, convex, white tablets, inscribed with SOMA 350

4 CONTRAINDICATIONS

SOMA is contraindicated in patients with a history of acute intermittent porphyria or a hypersensitivity reaction to a carbamate such as meprobamate.

5 WARNINGS AND PRECAUTIONS

5.1 Sedation

SOMA has sedative properties (in the low back pain trials, 13% to 17% of patients who received SOMA experienced sedation compared to 6% of patients who received placebo) [see ADVERSE REACTIONS (6.1)] and may impair the mental and/or physical abilities required for the performance of potentially hazardous tasks such as driving a motor vehicle or operating machinery. There have been post-marketing reports of motor vehicle accidents associated with the use of SOMA.

Since the sedative effects of SOMA and other CNS depressants (e.g., alcohol, benzodiazepines, opioids, tricyclic antidepressants) may be additive, appropriate caution should be exercised with patients who take more than one of these CNS depressants simultaneously.

5.2 Abuse, Dependence, and Withdrawal

Carisoprodol, the active ingredient in SOMA, has been subject to abuse, dependence, and withdrawal, misuse and criminal diversion [see Drug Abuse and Dependence (9.1, 9.2, 9.3)]. Abuse of SOMA poses a risk of overdosage which may lead to death, CNS and respiratory depression, hypotension, seizures and other disorders [see Overdosage (10)].

Post-marketing experience cases of carisoprodol abuse and dependence have been reported in patients with prolonged use and a history of drug abuse. Although most of these patients took other drugs of abuse, some patients solely abused carisoprodol. Withdrawal symptoms have been reported following abrupt cessation of SOMA after prolonged use. Reported withdrawal symptoms included insomnia, vomiting, abdominal cramps, headache, tremors, muscle twitching, ataxia, hallucinations, and psychosis. One of carisoprodol’s metabolites, meprobamate (a controlled substance), may also cause dependence [see Clinical Pharmacology (12.3)].

To reduce the risk of SOMA abuse assess the risk of abuse prior to prescribing. After prescribing, limit the length of treatment to three weeks for the relief of acute musculoskeletal discomfort, keep careful prescription records, monitor for signs of abuse and overdose, and educate patients and their families about abuse and on proper storage and disposal.

5.3 Seizures

There have been post-marketing reports of seizures in patients who received SOMA. Most of these cases have occurred in the setting of multiple drug overdoses (including drugs of abuse, illegal drugs, and alcohol) [see Overdosage (10)].

6 ADVERSE REACTIONS

6.1 Clinical Studies Experience

Because clinical studies are conducted under widely varying conditions, adverse reaction rates observed in clinical studies of a drug cannot be directly compared to rates in the clinical studies of another drug and may not reflect rates observed in practice.

The data described below are based on 1387 patients pooled from two double blind, randomized, multicenter, placebo controlled, one-week trials in adult patients with acute, mechanical, lower back pain [see Clinical Studies (14)]. In these studies, patients were treated with 250 mg of SOMA, 350 mg of SOMA, or placebo three times a day and at bedtime for seven days. The mean age was about 41 years old with 54% females and 46% males and 74 % Caucasian, 16 % Black, 9% Asian, and 2% other.

There were no deaths and there were no serious adverse reactions in these two trials. In these two studies, 2.7%, 2%, and 5.4%, of patients treated with placebo, 250 mg of SOMA, and 350 mg of SOMA, respectively, discontinued due to adverse events; and 0.5%, 0.5%, and 1.8% of patients treated with placebo, 250 mg of SOMA, and 350 mg of SOMA, respectively, discontinued due to central nervous system adverse reactions.

Table 1 displays adverse reactions reported with frequencies greater than 2% and more frequently than placebo in patients treated with SOMA in the two trials described above.

Table 1. Patients with Adverse Reactions in Controlled Studies
Adverse Reaction | Placebo (n=560) n (%) | SOMA 250 mg (n=548) n (%) | SOMA 350 mg (n=279) n (%)
Drowsiness | 31 (6) | 73 (13) | 47 (17)
Dizziness | 11 (2) | 43 (8) | 19 (7)
Headache | 11 (2) | 26 (5) | 9 (3)

6.2 Post-marketing Experience

The following events have been reported during postapproval use of SOMA. Because these reactions are reported voluntarily from a population of uncertain size, it is not always possible to reliably estimate their frequency or establish a causal relationship to drug exposure.

Cardiovascular: Tachycardia, postural hypotension, and facial flushing [see Overdosage (10)].
Central Nervous System: Drowsiness, dizziness, vertigo, ataxia, tremor, agitation, irritability, headache, depressive reactions, syncope, insomnia, and seizures [see Overdosage (10)].
Gastrointestinal: Nausea, vomiting, and epigastric discomfort.
Hematologic: Leukopenia, pancytopenia

7 DRUG INTERACTIONS

7.1 CNS Depressants

The sedative effects of SOMA and other CNS depressants (e.g., alcohol, benzodiazepines, opioids, tricyclic antidepressants) may be additive. Therefore, caution should be exercised with patients who take more than one of these CNS depressants simultaneously. Concomitant use of SOMA and meprobamate, a metabolite of SOMA, is not recommended [see Warnings and Precautions (5.1)].

7.2 CYP2C19 Inhibitors and Inducers

Carisoprodol is metabolized in the liver by CYP2C19 to form meprobamate [see Clinical Pharmacology (12.3) ]. Co-administration of CYP2C19 inhibitors, such as omeprazole or fluvoxamine, with SOMA could result in increased exposure of carisoprodol and decreased exposure of meprobamate. Co-administration of CYP2C19 inducers, such as rifampin or St. John’s Wort, with SOMA could result in decreased exposure of carisoprodol and increased exposure of meprobamate. Low dose aspirin also showed an induction effect on CYP2C19. The full pharmacological impact of these potential alterations of exposures in terms of either efficacy or safety of SOMA is unknown.

8 USE IN SPECIFIC POPULATIONS

8.1 Pregnancy

Risk Summary

Data over many decades of carisoprodol use in pregnancy have not identified a drug-associated risk of major birth defects, miscarriage, or other adverse maternal or fetal outcomes. Data on meprobamate, the primary metabolite of carisoprodol, also do not show a consistent association between maternal use of meprobamate and an increased risk of major birth defects (see Data).

In a published animal reproduction study, pregnant mice administered carisoprodol orally at 2.6- and 4.1-times the maximum recommended human dose ([MRHD] of 1400 mg per day [350 mg QID] based on body surface area [BSA] comparison) from gestation through weaning resulted in reduced fetal weights, postnatal weight gain, and postnatal survival (see Data).

The estimated background risk of major birth defects and miscarriage for the indicated population is unknown. All pregnancies have a background risk of birth defect, loss, or other adverse outcomes. In the U.S. general population, the estimated background risk of major birth defects and miscarriage in clinically recognized pregnancies is 2 to 4% and 15 to 20%, respectively.

Data

Human Data

Retrospective case-control and cohort studies of meprobamate use during the first trimester of pregnancy have not consistently identified an increased risk or pattern of major birth defects. For children exposed to meprobamate in-utero, one study found no adverse effect on mental or motor development or IQ scores.

Animal Data

Embryofetal development studies in animals have not been completed.

In a published pre- and post-natal development animal study, pregnant mice administered carisoprodol orally at 300, 750, or 1200 mg/kg/day (approximately 1-, 2.6-, and 4.1-times the MRHD based on BSA comparison) from 7-days prior to gestation through birth and from lactation through weaning resulted in reduced fetal weights, postnatal weight gain, and postnatal survival at 2.6- and 4.1-times the MRHD.

8.2 Lactation

Risk Summary

Data from published literature report that carisoprodol and its metabolite, meprobamate, are present in breastmilk. There are no data on the effect of carisoprodol on milk production. There is one report of sedation in an infant who was breastfed by a mother taking carisoprodol (see Clinical Considerations). Because there have been no consistent reports of adverse events in breastfed infants over decades of use, the developmental and health benefits of breastfeeding should be considered along with the mother’s clinical need for SOMA and any potential adverse effects on the breastfed infant from SOMA or from the underlying maternal condition.

Clinical Considerations

Infants exposed to SOMA through breast milk should be monitored for sedation.

8.4 Pediatric Use

The efficacy, safety, and pharmacokinetics of SOMA in pediatric patients less than 16 years of age have not been established.

8.5 Geriatric Use

The efficacy, safety, and pharmacokinetics of SOMA in patients over 65 years old have not been established.

8.6 Renal Impairment

The safety and pharmacokinetics of SOMA in patients with renal impairment have not been evaluated. Since SOMA is excreted by the kidney, caution should be exercised if SOMA is administered to patients with impaired renal function. Carisoprodol is dialyzable by hemodialysis and peritoneal dialysis.

8.7 Hepatic Impairment

The safety and pharmacokinetics of SOMA in patients with hepatic impairment have not been evaluated. Since SOMA is metabolized in the liver, caution should be exercised if SOMA is administered to patients with impaired hepatic function.

8.8 Patients with Reduced CYP2C19 Activity

Patients with reduced CYP2C19 activity have higher exposure to carisoprodol. Therefore, caution should be exercised in administration of SOMA to these patients [ see Clinical Pharmacology (12.3)].

9 DRUG ABUSE AND DEPENDENCE

9.1 Controlled Substance

SOMA contains carisoprodol, a Schedule IV controlled substance. Carisoprodol has been subject to abuse, misuse, and criminal diversion for nontherapeutic use [see Warnings and Precautions (5.2)].

9.2 Abuse

Abuse of carisoprodol poses a risk of overdosage which may lead to death, CNS and respiratory depression, hypotension, seizures and other disorders [see Warnings and Precautions (5.2) and Overdosage (10)]. Patients at high risk of SOMA abuse may include those with prolonged use of carisoprodol, with a history of drug abuse, or those who use SOMA in combination with other abused drugs.

Prescription drug abuse is the intentional non-therapeutic use of a drug, even once, for its rewarding psychological effects. Drug addiction, which develops after repeated drug abuse, is characterized by a strong desire to take a drug despite harmful consequences, difficulty in controlling its use, giving a higher priority to drug use than to obligations, increased tolerance, and sometimes physical withdrawal. Drug abuse and drug addiction are separate and distinct from physical dependence and tolerance (for example, abuse or addiction may not be accompanied by tolerance or physical dependence) [see Drug Abuse and Dependence (9.3)].

9.3 Dependence

Tolerance is when a patient’s reaction to a specific dosage and concentration is progressively reduced in the absence of disease progression, requiring an increase in the dosage to maintain the same. Physical dependence is characterized by withdrawal symptoms after abrupt discontinuation or a significant dose reduction of a drug. Both tolerance and physical dependence have been reported with the prolonged use of SOMA. Reported withdrawal symptoms with SOMA include insomnia, vomiting, abdominal cramps, headache, tremors, muscle twitching, anxiety, ataxia, hallucinations, and psychosis. Instruct patients taking large doses of SOMA or those taking the drug for a prolonged time to not abruptly stop SOMA [see Warnings and Precautions (5.2)].

10 OVERDOSAGE

Clinical Presentation

Overdosage of SOMA commonly produces CNS depression. Death, coma, respiratory depression, hypotension, seizures, delirium, hallucinations, dystonic reactions, nystagmus, blurred vision, mydriasis, euphoria, muscular incoordination, rigidity, and/or headache have been reported with SOMA overdosage. Serotonin syndrome has been reported with carisoprodol intoxication. Many of the carisoprodol overdoses have occurred in the setting of multiple drug overdoses (including drugs of abuse, illegal drugs, and alcohol). The effects of an overdose of carisoprodol and other CNS depressants (e.g., alcohol, benzodiazepines, opioids, tricyclic antidepressants) can be additive even when one of the drugs has been taken in the recommended dosage. Fatal accidental and non-accidental overdoses of SOMA have been reported alone or in combination with CNS depressants.

Treatment of Overdosage

Basic life support measures should be instituted as dictated by the clinical presentation of the SOMA overdose. Vomiting should not be induced because of the risk of CNS and respiratory depression, and subsequent aspiration. Circulatory support should be administered with volume infusion and vasopressor agents if needed. Seizures should be treated with intravenous benzodiazepines and the reoccurrence of seizures may be treated with phenobarbital. In cases of severe CNS depression, airway protective reflexes may be compromised and tracheal intubation should be considered for airway protection and respiratory support.

For decontamination in cases of severe toxicity, activated charcoal should be considered in a hospital setting in patients with large overdoses who present early and are not demonstrating CNS depression and can protect their airway.

For more information on the management of an overdose of SOMA, contact a Poison Control Center.

11 DESCRIPTION

SOMA (carisoprodol) Tablets are available as 250 mg and 350 mg round, white tablets. Carisoprodol is a white, crystalline powder, having a mild, characteristic odor and a bitter taste. It is slightly soluble in water; freely soluble in alcohol, in chloroform, and in acetone; and its solubility is practically independent of pH. Carisoprodol is present as a racemic mixture. Chemically, carisoprodol is (±)-2-Methyl-2-propyl-1,3-propanediol carbamate isopropylcarbamate and the molecular formula is C12H24N2O4, with a molecular weight of 260.33. The structural formula is:

Other ingredients in the SOMA drug product include alginic acid, magnesium stearate, potassium sorbate, starch, and tribasic calcium phosphate.

12 CLINICAL PHARMACOLOGY

12.1 Mechanism of Action

The mechanism of action of carisoprodol in relieving discomfort associated with acute painful musculoskeletal conditions has not been clearly identified.

In animal studies, muscle relaxation induced by carisoprodol is associated with altered interneuronal activity in the spinal cord and in the descending reticular formation of the brain.

12.2 Pharmacodynamics

Carisoprodol is a centrally acting skeletal muscle relaxant that does not directly relax skeletal muscles.

A metabolite of carisoprodol, meprobamate, has anxiolytic and sedative properties. The degree to which these properties of meprobamate contribute to the safety and efficacy of SOMA is unknown.

12.3 Pharmacokinetics

Absorption

The pharmacokinetics of carisoprodol and its metabolite meprobamate were studied in a crossover study of 24 healthy subjects (12 male and 12 female) who received single doses of 250 mg and 350 mg SOMA (see Table 2). The exposure of carisoprodol and meprobamate was dose proportional between the 250 mg and 350 mg doses. The Cmax of meprobamate was 2.5 ± 0.5 μg/mL (mean ± SD) after administration of a single 350 mg dose of SOMA, which is approximately 30% of the Cmax of meprobamate (approximately 8 μg/mL) after administration of a single 400 mg dose of meprobamate.

Table 2. Pharmacokinetic Parameters of Carisoprodol and Meprobamate (Mean ± SD, n=24)
 | 250 mg SOMA | 350 mg SOMA
 | Carisoprodol
Cmax (μg/mL) | 1.2 ± 0.5 | 1.8 ± 1.0
AUCinf (μg*hr/mL) | 4.5 ± 3.1 | 7.0 ± 5.0
Tmax (hr) | 1.5 ± 0.8 | 1.7 ± 0.8
T1/2 (hr) | 1.7 ± 0.5 | 2.0 ± 0.5
 | Meprobamate
Cmax (μg/mL) | 1.8 ± 0.3 | 2.5 ± 0.5
AUCinf (μg*hr/mL) | 32 ± 6.2 | 46 ± 9.0
Tmax (hr) | 3.6 ± 1.7 | 4.5 ± 1.9
T1/2 (hr) | 9.7 ± 1.7 | 9.6 ± 1.5

Absolute bioavailability of carisoprodol has not been determined. The mean time to peak plasma concentrations (Tmax) of carisoprodol was approximately 1.5 to 2 hours.

Food Effect

Co-administration of a high-fat meal with SOMA (350 mg tablet) had no effect on the pharmacokinetics of carisoprodol. Therefore, SOMA may be administered with or without food.

Elimination

Metabolism

The major pathway of carisoprodol metabolism is via the liver by cytochrome enzyme CYP2C19 to form meprobamate. This enzyme exhibits genetic polymorphism (see Patients with Reduced CYP2C19 Activity below).

Excretion

Carisoprodol is eliminated by both renal and non-renal routes with a terminal elimination half-life of approximately 2 hours. The half-life of meprobamate is approximately 10 hours.

Specific Populations

Sex

Exposure of carisoprodol is higher in female than in male subjects (approximately 30-50% on a weight adjusted basis). Overall exposure of meprobamate is comparable between female and male subjects.

Patients with Reduced CYP2C19 Activity

SOMA should be used with caution in patients with reduced CYP2C19 activity. Published studies indicate that patients who are poor CYP2C19 metabolizers have a 4-fold increase in exposure to carisoprodol, and concomitant 50% reduced exposure to meprobamate compared to normal CYP2C19 metabolizers. The prevalence of poor metabolizers in Caucasians and African Americans is approximately 3-5% and in Asians is approximately 15-20%.

13 NONCLINICAL TOXICOLOGY

13.1 Carcinogenesis, Mutagenesis, Impairment of Fertility

Carcinogenesis

Long term studies in animals have not been performed to evaluate the carcinogenic potential of carisoprodol.

Mutagenesis

SOMA was not formally evaluated for genotoxicity. In published studies, carisoprodol was mutagenic in the in vitro mouse lymphoma cell assay in the absence of metabolizing enzymes, but was not mutagenic in the presence of metabolizing enzymes. Carisoprodol was clastogenic in the in vitro chromosomal aberration assay using Chinese hamster ovary cells with or without the presence of metabolizing enzymes. Other types of genotoxic tests resulted in negative findings. Carisoprodol was not mutagenic in the Ames reverse mutation assay using S. typhimurium strains with or without metabolizing enzymes, and was not clastogenic in an in vivo mouse micronucleus assay of circulating blood cells.

Impairment of Fertility

SOMA was not formally evaluated for effects on fertility. A published reproductive study in which female mice received carisoprodol orally at doses of 300, 750, or 1200 mg/kg/day (approximately 1, 2.6, and 4.1 times the MRHD of 1400 mg per day [350 mg QID] based on body surface area [BSA] comparison) from 1-week prior to mating, to 27-weeks post-mating found no alteration in fertility although an alteration in reproductive cycles characterized by a greater time spent in estrus was observed at a carisoprodol dose of 1200 mg/kg/day. In a 13-week toxicology study that did not determine fertility, mouse testes weight and sperm motility were reduced at a dose of 1200 mg/kg/day (maternal doses equivalent to 4.2-times the MRHD based on BSA comparison). In both studies, the no effect level was 750 mg/kg/day, corresponding to approximately 2.6-times the MRHD based on a BSA comparison. The significance of these findings for human fertility is not known.

14 CLINICAL STUDIES

The safety and efficacy of SOMA for the relief of acute, idiopathic mechanical low back pain was evaluated in two, 7-day, double blind, randomized, multicenter, placebo controlled, U.S. trials (Studies 1 and 2). Patients had to be 18 to 65 years old and had to have acute back pain (≤ 3 days of duration) to be included in the trials. Patients with chronic back pain; at increased risk for vertebral fracture (e.g., history of osteoporosis); with a history of spinal pathology (e.g., herniated nucleus pulposus, spondylolisthesis or spinal stenosis); with inflammatory back pain, or with evidence of a neurologic deficit were excluded from participation. Concomitant use of analgesics (e.g., acetaminophen, NSAIDs, tramadol, opioid agonists), other muscle relaxants, botulinum toxin, sedatives (e.g., barbiturates, benzodiazepines, promethazine hydrochloride), and anti-epileptic drugs was prohibited.

In Study 1, patients were randomized to one of three treatment groups (i.e., SOMA 250 mg, SOMA 350 mg, or placebo) and in Study 2 patients were randomized to two treatment groups (i.e., SOMA 250 mg or placebo). In both studies, patients received study medication three times a day and at bedtime for seven days.

The primary endpoints were the relief from starting backache and the global impression of change, as reported by patients, on Study Day 3. Both endpoints were scored on a 5-point rating scale from 0 (worst outcome) to 4 (best outcome) in both studies. The primary statistical comparison was between the SOMA 250 mg and placebo groups in both studies.

The proportion of patients who used concomitant acetaminophen, NSAIDs, tramadol, opioid agonists, other muscle relaxants, and benzodiazepines was similar in the treatment groups.

The results for the primary efficacy evaluations in the acute, low back pain studies are presented in Table 3.

Table 3. Results of the Primary Efficacy Endpoints [The primary efficacy endpoints (Relief from Starting Backache and Global Impression of Change) were assessed by the patients on Study Day 3. These endpoints were scored on a 5-point rating scale from 0 (worst outcome) to 4 (best outcome).] in Studies 1 and 2
Study | Parameter | Placebo | SOMA 250 mg | SOMA 350 mg
1 | Number of Patients | n=269 | n=264 | n=273
1 | Relief from Starting Backache, Mean (SE) [Mean is the least squared mean and SE is the standard error of the mean. The ANOVA model was used for the primary statistical comparison between the SOMA 250 mg and placebo groups.] | 1.4 (0.1) | 1.8 (0.1) | 1.8 (0.1)
1 | Difference between SOMA and Placebo, Mean (SE) (95% CI) |  | 0.4 (0.2, 0.5) | 0.4 (0.2, 0.6)
1 | Global Impression of Change, Mean (SE) | 1.9 (0.1) | 2.2 (0.1) | 2.2 (0.1)
1 | Difference between SOMA and Placebo, Mean (SE) (95% CI) |  | 0.2 (0.1, 0.4) | 0.3 (0.1, 0.4)
2 | Number of Patients | n=278 | n=269
2 | Relief from Starting Backache, Mean (SE) | 1.1 (0.1) | 1.8 (0.1)
2 | Difference between SOMA and Placebo, Mean (SE) (95% CI) |  | 0.7 (0.5, 0.9)
2 | Global Impression of Change, Mean (SE) | 1.7 (0.1) | 2.2 (0.1)
2 | Difference between SOMA and Placebo, Mean (SE) (95% CI) |  | 0.5 (0.4, 0.7)

Patients treated with SOMA experienced improvement in function as measured by the Roland-Morris Disability Questionnaire (RMDQ) score on Days 3 and 7.

16 HOW SUPPLIED/STORAGE AND HANDLING

250 mg Tablets: round, convex, white tablets, inscribed with SOMA 250; available in bottles of 100 (NDC 0037-2250-10) and bottles of 30 (NDC 0037-2250-30).

350 mg Tablets: round, convex, white tablets, inscribed with SOMA 350; available in bottles of 100 (NDC 0037-2001-01).

Storage
Store at controlled room temperature 20° - 25°C (68° - 77°F).

17 PATIENT COUNSELING INFORMATION

Patients should be advised to contact their physician if they experience any adverse reactions to SOMA.

Sedation

Advise patients that SOMA may cause drowsiness and/or dizziness, and has been associated with motor vehicle accidents. Patients should be advised to avoid taking SOMA before engaging in potentially hazardous activities such as driving a motor vehicle or operating machinery [see Warnings and Precautions (5.1)].

Avoidance of Alcohol and Other CNS Depressants

Advise patients to avoid alcoholic beverages while taking SOMA and to check with their doctor before taking other CNS depressants such as benzodiazepines, opioids, tricyclic antidepressants, sedating antihistamines, or other sedatives [see Warnings and Precautions (5.1)].

SOMA Should Only Be Used for Short-Term Treatment

Advise patients that treatment with SOMA should be limited to acute use (up to two or three weeks) for the relief of acute, musculoskeletal discomfort. In the post-marketing experience with SOMA, cases of dependence, withdrawal, and abuse have been reported with prolonged use. If the musculoskeletal symptoms still persist, patients should contact their healthcare provider for further evaluation.

Lactation

Advise nursing mothers using SOMA to monitor neonates for signs of sedation [see Use in Specific Populations (8.2)].

For more information, call Viatris at 1-877-446-3679 (1-877-4-INFO-RX).

SOMA is a registered trademark of Meda Pharmaceuticals Inc., a Viatris Company.

© 2025 Viatris Inc.

Distributed by:
Viatris Specialty LLC
Morgantown, WV 26505 U.S.A.

Revised: 8/2025

201112-01

VS:SOV:SOMT:R1

PRINCIPAL DISPLAY PANEL – 250 mg

NDC 0037-2250-30

30 Tablets

Soma® CIV
Carisoprodol Tablets, USP
250 mg

Rx Only

Viatris

Please see enclosed full Prescribing
Information.

Dispense in tight container.
Store at controlled room temperature
20°-25°C (68°-77°F).

Distributed by:
Viatris Specialty LLC
Morgantown, WV 26505 U.S.A

VSSOV2250H1 Rev. 8/2025

200997-01

PRINCIPAL DISPLAY PANEL – 350 mg

NDC 0037-2001-01

100 Tablets

Soma® CIV
Carisoprodol Tablets, USP
350 mg

Rx Only

Viatris

Package circular attached.

Usual adult dosage: 1 tablet
three times daily and at bedtime.

Dispense in tight container.
Store at controlled room
temperature 20°-25°C (68°-77°F).

Distributed by:
Viatris Specialty LLC
Morgantown, WV 26505 U.S.A

VSSOV2001A1 Rev. 8/2025

200998-01